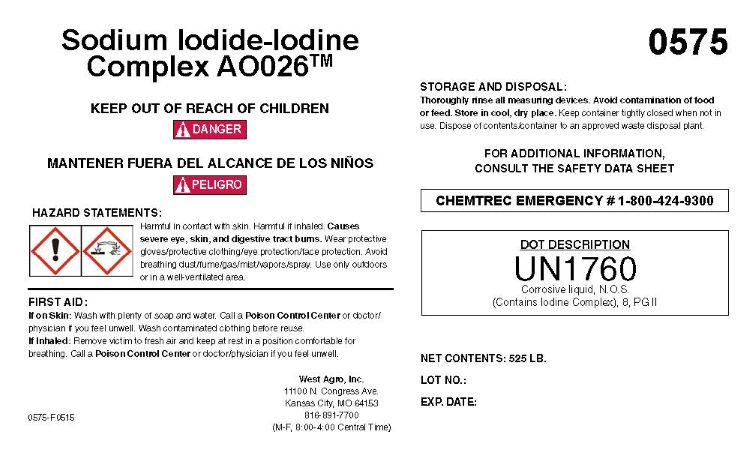 DRUG LABEL: Sodium Iodide-Iodine Complex AO026
NDC: 55756-781 | Form: SOLUTION
Manufacturer: DeLval, Inc
Category: other | Type: BULK INGREDIENT - ANIMAL DRUG
Date: 20260125

ACTIVE INGREDIENTS: IODINE 1 kg/1 kg
INACTIVE INGREDIENTS: WATER; FORMIC ACID; SODIUM HYDROXIDE

Sodium Iodide-lodine Complex AO026

KEEP OUT OF REACH OF CHILDREN! DANGER

-

HAZARD STATEMENTS:

Harmful in contact with skin. Harmful if inhaled. Causes severe eye, skin, and digestive tract burns. Wesr protective gloves/protective clothing/eye protection/face protection. Avoid breathing dust/fume/gas/mist/vapors/spray. Use only outdoors or in a vell-ventilated area.

FIRST AID:

If on Skin: Wash with plenty of soap and water. Call a Poison Control Centrer or doctor/physician if you feel unwell. Wash contaminated clothing before resue.

If Inhaled: Remove victim to fresh air and keep at rest in a position comfortable for breathing. Call a Poison Control Center or doctor/physician if you feel unwell.

STORAGE AND DISPOSAL

Thoroughly rinse all measuring devices. Avoid contamination of food or feed. Store in cool, dry place. Keep container tightly closed when not in use. Dispose of contents/container to an approved waste disposal plant.

FOR ADDITIONAL INFORMATION CONSULT THE SAFETY DATA SHEET

CHEMTREC EMERGENCY # 1-800-424-9300

DOT DECRIPTION

UN1760

Corrosive liquid, N.O.S.

(Contains Iodine Complex), 8, PG II

HOW SUPPLIED

West Agro, Inc.

11100 N. Congress Ave.

Kansas City, MO 64153

816-891-7700

(M-F, 8:00-4:00 Central time)